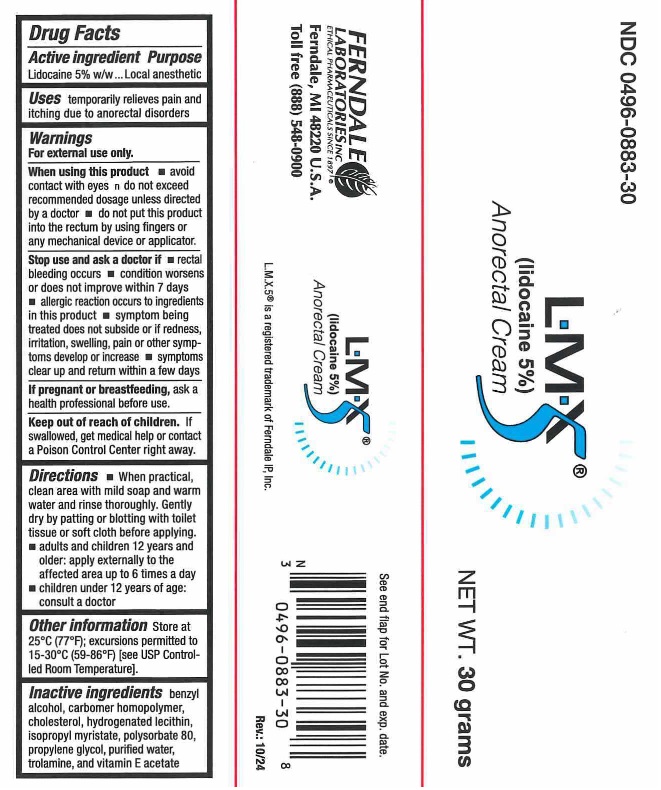 DRUG LABEL: LMX5
NDC: 0496-0883 | Form: CREAM
Manufacturer: Ferndale Laboratories, Inc.
Category: otc | Type: HUMAN OTC DRUG LABEL
Date: 20251210

ACTIVE INGREDIENTS: LIDOCAINE 50 mg/1 g
INACTIVE INGREDIENTS: BENZYL ALCOHOL; CARBOMER HOMOPOLYMER TYPE C; CHOLESTEROL; LECITHIN, SOYBEAN; ISOPROPYL MYRISTATE; POLYSORBATE 80; PROPYLENE GLYCOL; WATER; TROLAMINE; ALPHA-TOCOPHEROL ACETATE

LMX5 (lidocaine 5%) Anorectal Cream

Active ingredient

Lidocaine 5% w/w

Purpose

Local anesthetic

Uses

temporarily relieves pain and itching due to anorectal disorders

Warnings

When using this product

- avoid contact with eyes
- do not exceed recommended dosage unless directed by a doctor

Stop use and ask a doctor if

- rectal bleeding occurs
- condition worsens or does not improve within 7 days
- allergic reaction occurs
- redness, irritation, swelling, pain or other symptoms begin or increase
- symptoms clear up and return within a few days

Keep out of reach of children.

If swallowed, get medical help or contact a Poison Control Center right away.

Directions

- When practical, clean area with mild soap and warm water and rinse thoroughly. Gently dry by patting or blotting with toilet tissue or soft cloth before applying.
- Adults and Children 12 years and older: Apply to the affected area up to 6 times a day.
- Children under 12 years of age: Consult a doctor.

Other information

Store at 25°C (77°F); excursions permitted to 15-30°C (59-86°F) [see USP Controlled Room Temperature].

Inactive Ingredients

benzyl alcohol, carbomer homopolymer, chloesterol, hydrogenated lecithin, isopropyl myristate, polysorbate 80, propylene glycol, purified water, trolamine, and vitamin E acetate

Package Label

Manufactured for Ferndale Healthcare Inc.

Ferndale, MI 48220 U.S.A.

Toll free (888) 548-0900

www.ferndalehealthcare.com

L.M.X.5® is a registered trademark of Ferndale, IP Inc.
30 gram NDC 0496-0883-30